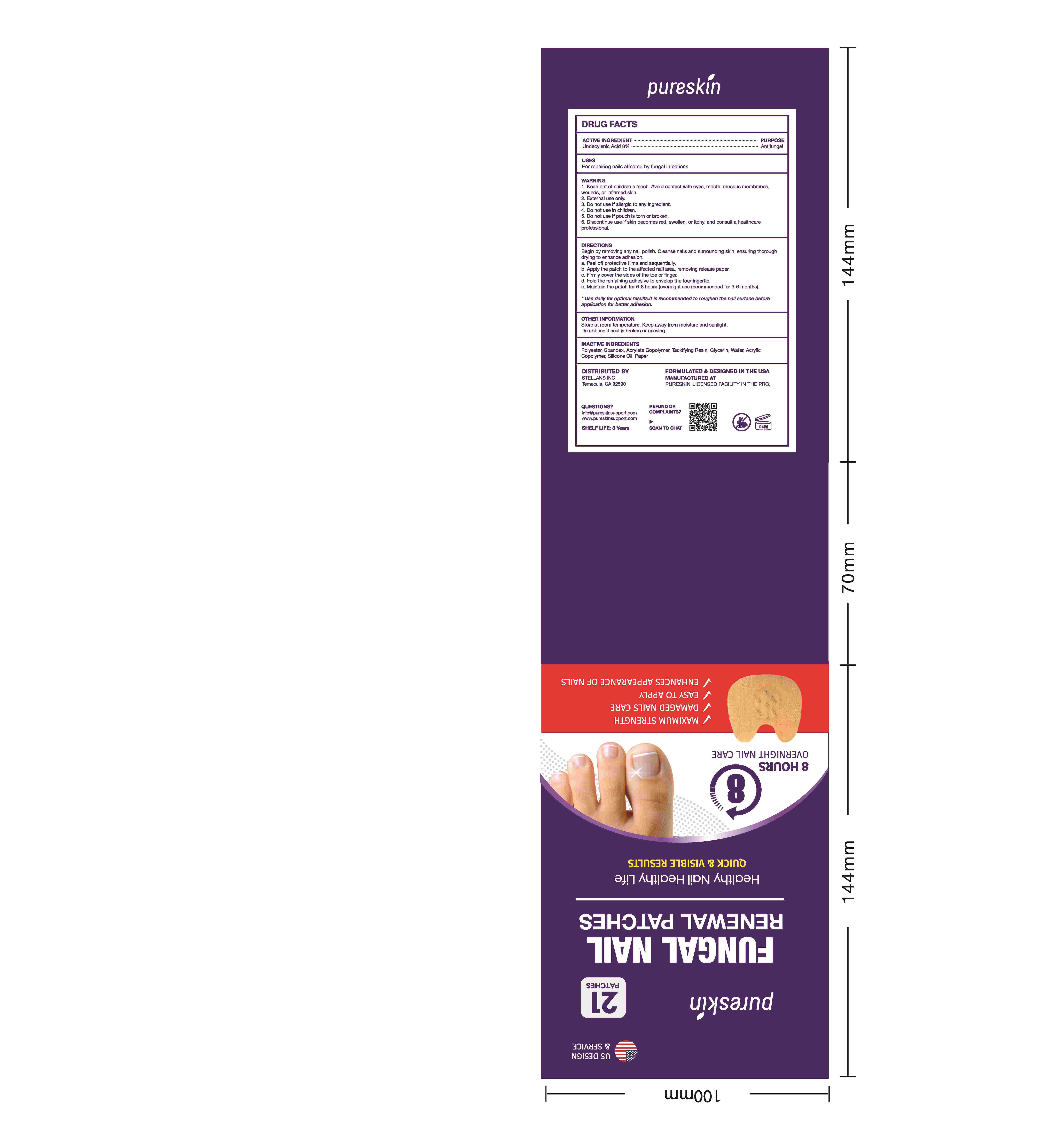 DRUG LABEL: Pureskin FUNGAL NAIL RENEWAL PATCHES
NDC: 84746-006 | Form: PATCH
Manufacturer: Shandong Yuyaotang Pharmaceutical Co., Ltd
Category: otc | Type: HUMAN OTC DRUG LABEL
Date: 20241212

ACTIVE INGREDIENTS: UNDECYLENIC ACID 8 g/100 1
INACTIVE INGREDIENTS: GLYCERIN; IVERMECTIN; DICLORAN; BUTYL ACRYLATE/METHYL METHACRYLATE/METHACRYLIC ACID COPOLYMER (18000 MW); POWDERED CELLULOSE; ACRYLIC ACID; ARCHANGELENONE; POLYESTER-7; WATER

84746-006 COMPLETED

Active Ingredient

Undecylenic Acid 8%

Purpose

Antifungal

Use

For repairing nails affected by fungal infections

Warnings

1. Keep out of children's reach. Avoid contact with eyes, mouth, mucous membranes, wounds, or inflamed skin.
2. External use only.
3. Do not use if allergic to any ingredient.
4. Do not use in children.
5. Do not use if pouch is torn or broken.
6. Discontinue use if skin becomes red, swollen, or itchy, and consult a healthcare professional.

Directions

Begin by removing any nail polish. Cleanse nails and surrounding skin, ensuring thorough drying to enhance adhesion.
a. Peel off protective films and sequentially.
b. Apply the patch to the affected nail area, removing release paper.
c. Firmly cover the sides of the toe or finger.
d. Fold the remaining adhesive to envelop the toe/fingertip.
e. Maintain the patch for 6-8 hours (overnight use recommended for 3-6 months).
Use daily for optimal results. It is recommended to roughen the nail surface before application for better adhesion.

Other information

Store at room temperature. Keep away from moisture and sunlight.
Do not use if seal is broken or missing.

Inactive ingredients

Polyester, Spandex, Acrylate Copolymer, Tackifying Resin, Glycerin, Water, Acrylic Copolymer, Silicone Oil, Paper

Questions

info@pureskinsupport.com
www.pureskinsupport.com